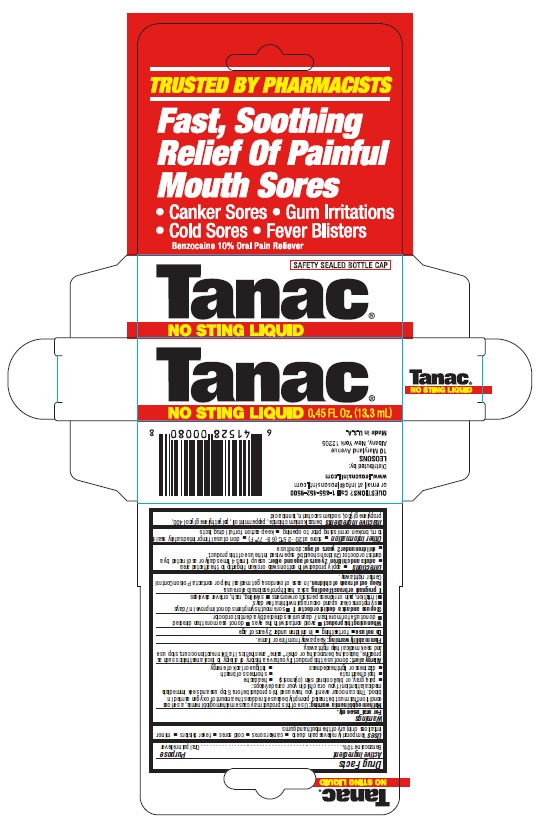 DRUG LABEL: TANAC Oral Pain Reliever
NDC: 69626-0049 | Form: LIQUID
Manufacturer: Leosons Overseas Corp
Category: otc | Type: HUMAN OTC DRUG LABEL
Date: 20241115

ACTIVE INGREDIENTS: BENZOCAINE 10 g/100 mL
INACTIVE INGREDIENTS: SACCHARIN SODIUM; TANNIC ACID; PEPPERMINT OIL; PROPYLENE GLYCOL; BENZALKONIUM CHLORIDE; POLYETHYLENE GLYCOL 400

TANAC Oral Pain Reliever

Active Ingredients & Purposes

Active Ingredient | Purpose
Benzocaine 10%........................................................ | Oral pain reliever

Uses

Temporarily relieves pain due to

- canker sores
- cold sores
- fever blisters
- minor irritations or injury of the mouth and gums

Warnings

For oral use only.

WARNINGS

Methemoglobinemia warning: Use of this product may cause methemoglobinemia, a serious
condition that must be treated promptly because it reduces the amount of oxygen carried in
blood. This can occur even if you have used this product before. Stop use and seek immediate
medical attention if you or a child in your care develops:

- pale, gray, or blue colored skin (cyanosis)
- headache
- rapid heart rate
- shortness of breath
- dizziness or lightheadedness
- fatigue or lack of energy

Allergy alert: do not use this product if you have a history of allergy to local anesthetics such as
procaine, butacaine, benzocaine, or other “caine” anesthetics. If a skin reaction occurs, stop use
and seek medical help right away.

WARNINGS

Flammability warning: Keep away from fire or flame.

Stop use and ask a doctor or dentist if

- sore mouth symptoms do not improve in 7 days
- symptoms clear up and occur again within a few days
- irritation, pain or redness persists or worsens swelling, rash, or fever develops

If pregnant or breast-feeding,

ask a health professional before use.

Do not use

- for teething
- in children under 2 years of age

When using this product

- avoid contact with the eyes
- do not use more than directed
- do not use for more than 7 days unless directed by a dentist or doctor

Keep out of reach of children.

In case of overdose, get medical help or contact a Poison Control Center right away.

Directions

- apply product with cotton swab or clean fingertip to the affected area
- adults and children 2 years of age and older: use up times 4 times daily or as directed by a

dentist or doctor. Children should be supervised in the use of this product.

- children under 2 years of age: do not use

Other information

- store at 20 - 25°C (68 - 77°F)
- do not use if imprinted safety seal is torn, broken or missing prior to opening
- keep carton for full drug facts

Inactive ingredients

benzalkonium chloride, peppermint oil, polyethylene glycol 400, propylene glycol, sodium saccharin, tannic acid

Questions?

1-855-452-9500 or email at info@leosonsintl.com

Principal Display Panel

- canker sores
- gum irritations
- cold sores
- fever blisters

Tanac ®

Benzocaine 10%

Oral Pain Reliever

NO STING LIQUID

0.45 FL Oz. (13.3mL)